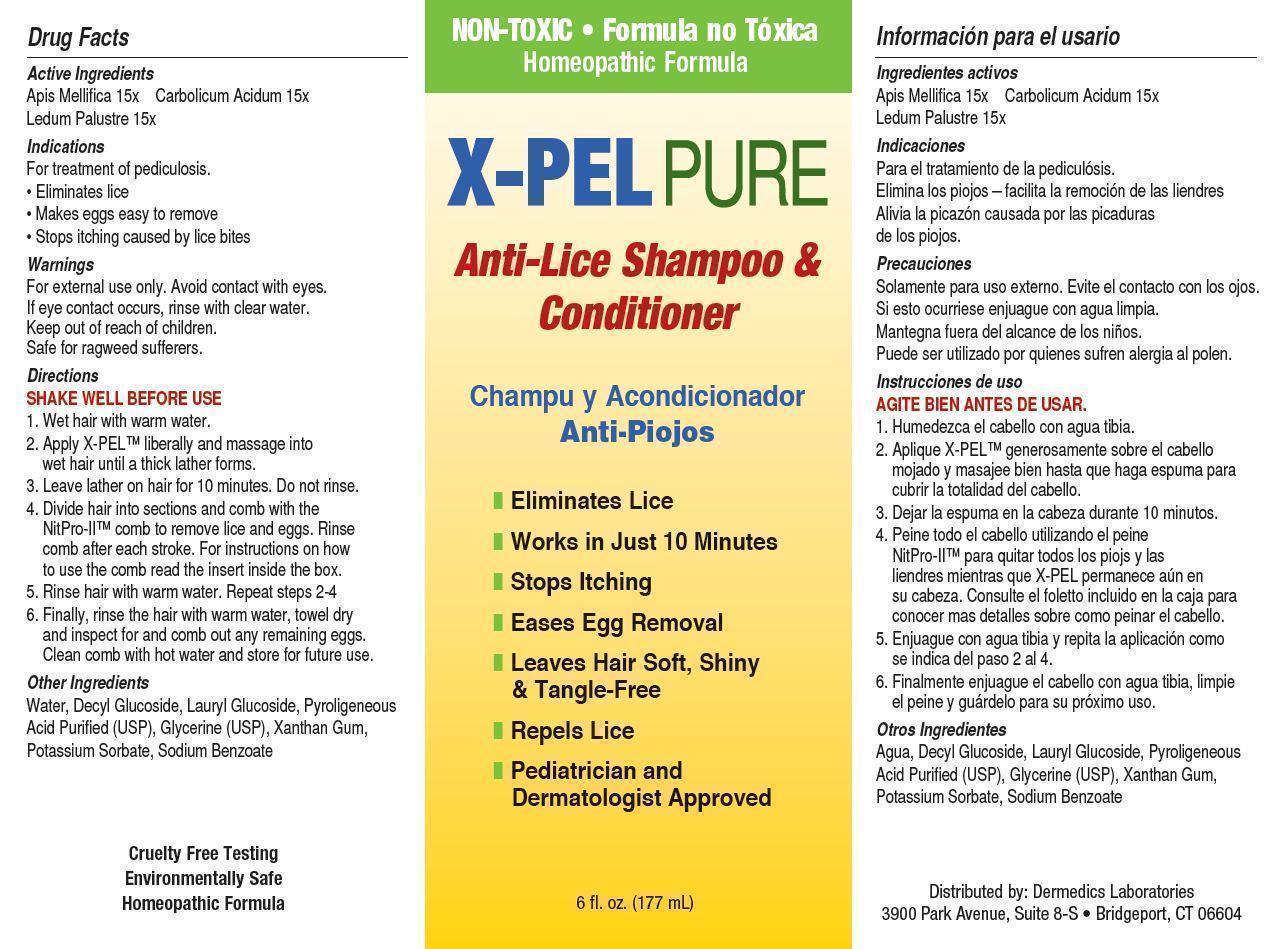 DRUG LABEL: X-PEL PURE Anti-Lice
NDC: 68971-002 | Form: SHAMPOO
Manufacturer: Briangelis Beauty Entps Corp
Category: homeopathic | Type: HUMAN OTC DRUG LABEL
Date: 20140716

ACTIVE INGREDIENTS: APIS MELLIFERA 15 [hp_X]/170 g; PHENOL 15 [hp_X]/170 g; LEDUM PALUSTRE TWIG 15 [hp_X]/170 g
INACTIVE INGREDIENTS: WATER; DECYL GLUCOSIDE; PYROLIGNEOUS ACID; LAURYL GLUCOSIDE; GLYCERIN; XANTHAN GUM; POTASSIUM SORBATE; SODIUM BENZOATE

Active Ingredients

Apis Mellifica 15x

Carbolicum Acidum 15x

Ledum Palustre 15x

PURPOSE

NON-TOXIC

Professional Formula

X-PEL PURE

Anti-Lice Shampoo & Conditioner

- Eliminates Lice
- Works in Just 10 Minutes
- Stops Itching
- Eases Egg Removal
- Leaves Hair Soft, Shiny & Tangle-Free
- Repels Lice
- Pediatrician and Dermatologist Approved

6 fl. oz. (177 mL)

Keep out of reach of children.

Indications

For treatment of pediculosis.

- Eliminates Lice
- Makes eggs easy to remove
- Stops itching caused by lice bites

Warnings

For external use only. Avoid contact with eyes.

If eye contact occurs, rinse with clear water.

Keep out of reach of children.

Safe for ragweed sufferers.

Directions

SHAKE WELL BEFORE USE

1. Wet hair with warm water.

2. Apply X-PEL™ liberally and massage into wet hair until a thick lather forms.

3. Leave lather on hair for 10 minutes. Do not rinse.

4. Divide hair into sections and comb with the NitPro-II™ comb to remove lice and eggs. Rinse comb after each stroke. For instructions on how to use the comb read the insert inside the box.

5. Rinse hair with warm water. Repeat steps 2-4.

6. Finally, rinse the hair with warm water, towel dry and inspect for and comb out any remaining eggs. Clean comb with hot water and store for future use.

INACTIVE INGREDIENT

Other ingredients

water, decyl glucoside, lauryl glucoside, pyroligeneous acid purified (USP), glycerine (USP), xanthan gum, potassium sorbate, sodium benzoate

OTHER SAFETY INFORMATION

Cruelty Free Testing

Environmentally Safe

Homeopathic Formula

Distributed By: Dermedics Laboratories

3900 Park Avenue, Suite 8-S, Bridgeport, CT 06604